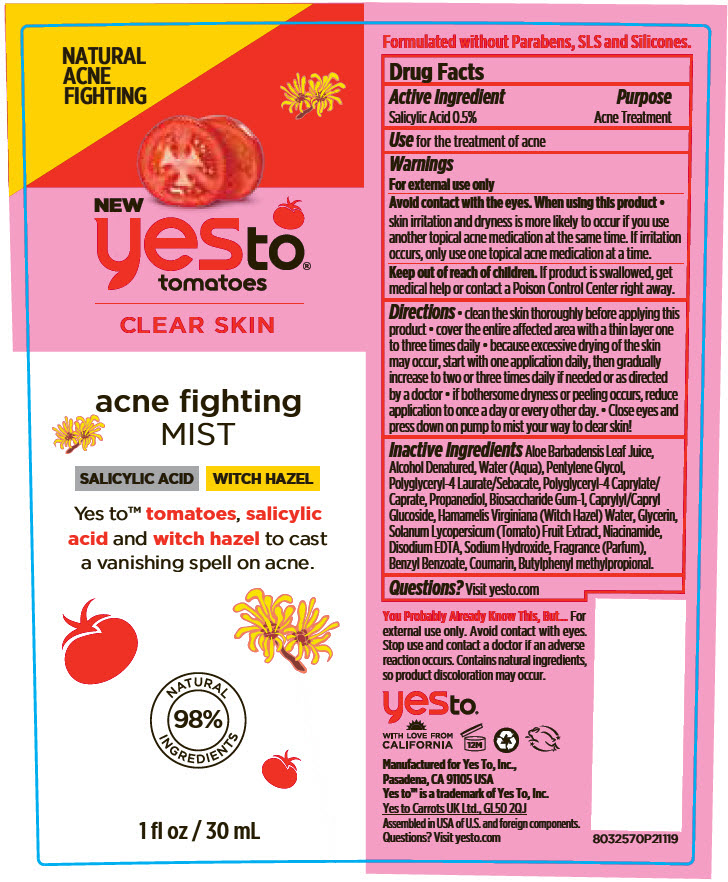 DRUG LABEL: Yes To Tomatoes Acne Fighting Mist
NDC: 69840-017 | Form: SPRAY
Manufacturer: Yes To Incorporated
Category: otc | Type: HUMAN OTC DRUG LABEL
Date: 20190429

ACTIVE INGREDIENTS: Salicylic Acid 5 mg/1 mL
INACTIVE INGREDIENTS: WATER; Pentylene Glycol; Polyglycerin-4; Polyglyceryl-4 Caprate; GLYCERIN; Biosaccharide Gum-1; Caprylyl/Capryl Oligoglucoside; Witch Hazel; Niacinamide; Edetate Disodium Anhydrous; PROPANEDIOL; ALOE VERA LEAF; Alcohol; SOLANUM LYCOPERSICUM FRUITING TOP; SODIUM HYDROXIDE

Yes To® Tomatoes Acne Fighting Mist

Drug Facts

Active Ingredient

Salicylic Acid 0.5%

Purpose

Acne Treatment

Use

for the treatment of acne

Warnings

For external use only

Avoid contact with the eyes.

When using this product

- skin irritation and dryness is more likely to occur if you use another topical acne medication at the same time. If irritation occurs, only use one topical acne medication at a time.

Keep out of reach of children. If product is swallowed, get medical help or contact a Poison Control Center right away.

Directions

- clean the skin thoroughly before applying this product
- cover the entire affected area with a thin layer one to three times daily
- because excessive drying of the skin may occur, start with one application daily, then gradually increase to two or three times daily if needed or as directed by a doctor
- if bothersome dryness or peeling occurs, reduce application to once a day or every other day.
- Close eyes and press down on pump to mist your way to clear skin!

Inactive Ingredients

Aloe Barbadensis Leaf Juice, Alcohol Denatured, Water (Aqua), Pentylene Glycol, Polyglyceryl-4 Laurate/Sebacate, Polyglyceryl-4 Caprylate/Caprate, Propanediol, Biosaccharide Gum-1, Caprylyl/Capryl Glucoside, Hamamelis Virginiana (Witch Hazel) Water, Glycerin, Solanum Lycopersicum (Tomato) Fruit Extract, Niacinamide, Disodium EDTA, Sodium Hydroxide, Fragrance (Parfum), Benzyl Benzoate, Coumarin, Butylphenyl methylpropional.

Questions?

Visit yesto.com

PRINCIPAL DISPLAY PANEL - 30 mL Bottle Label

NATURAL
ACNE
FIGHTING

NEW
yesto®
tomatoes

CLEAR SKIN

acne fighting
MIST

SALICYLIC ACID
WITCH HAZEL

Yes to™ tomatoes, salicylic
acid and witch hazel to cast
a vanishing spell on acne.

NATURAL
98%
INGREDIENTS

1 fl oz / 30 mL